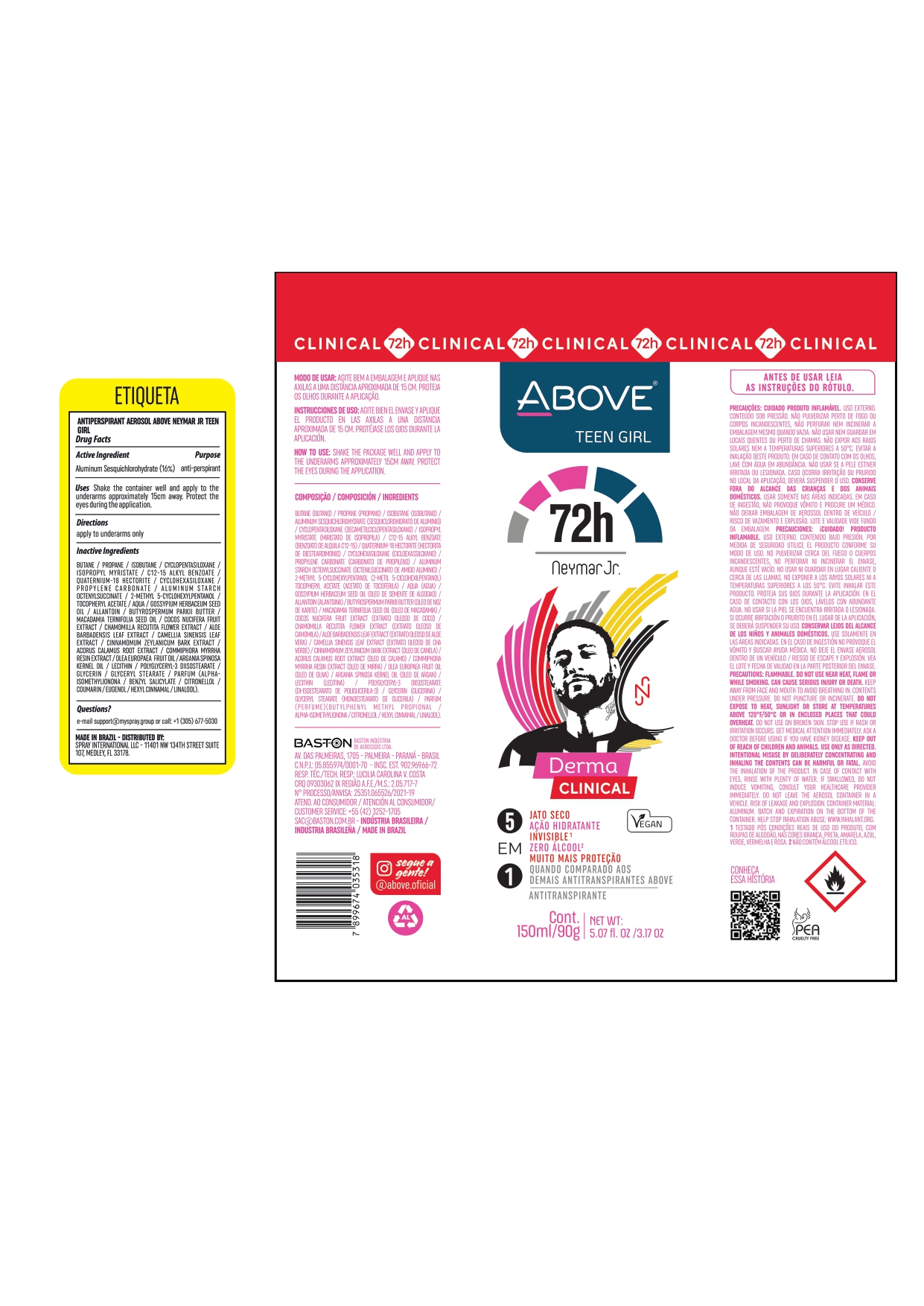 DRUG LABEL: ANTIPERSPIRANT ABOVE NEYMAR JR TEEN GIRL
NDC: 73306-1129 | Form: AEROSOL
Manufacturer: BASTON INDUSTRIA DE AEROSSOIS LTDA
Category: otc | Type: HUMAN OTC DRUG LABEL
Date: 20241009

ACTIVE INGREDIENTS: ALUMINUM SESQUICHLOROHYDRATE 16 g/100 g
INACTIVE INGREDIENTS: 2-METHYL 5-CYCLOHEXYLPENTANOL; ALKYL (C12-15) BENZOATE; CYCLOMETHICONE 6; PROPANE; CYCLOMETHICONE 5; WATER; LEVANT COTTONSEED OIL; .ALPHA.-TOCOPHEROL ACETATE; ALLANTOIN; ISOBUTANE; ISOPROPYL MYRISTATE; ALUMINUM STARCH OCTENYLSUCCINATE; BUTANE

ANTIPERSPIRANT ABOVE NEYMAR JR TEEN GIRL

ALUMINUM SESQUICHLOROHYDRATE 16 %

deodorant antiperspirant

SHAKE WELL AND APPLY TO THE ARMPITS FROM A DISTANCE OF ABOUT 15 CM. PROTECT YOUR EYES DURING APPLICATION

INACTIVE INGREDIENT

BUTANE
PROPANE
ISOBUTANE
CYCLOPENTASILOXANE
ISOPROPYL MYRISTATE
C12-15 ALKYL BENZOATE
PARFUM
QUATERNIUM-18 HECTORITE
CYCLOHEXASILOXANE
PROPYLENE CARBONATE
ALUMINUM STARCH OCTENYLSUCCINATE
2-METHYL 5-CYCLOHEXYLPENTANOL
TOCOPHERYL ACETATE
AQUA
GOSSYPIUM HERBACEUM SEED OIL
ALLANTOIN
BUTYROSPERMUM PARKII BUTTER
MACADAMIA TERNIFOLIA SEED OIL
COCOS NUCIFERA FRUIT EXTRACT
CHAMOMILLA RECUTITA FLOWER EXTRACT
ALOE BARBADENSIS LEAF EXTRACT
CAMELLIA SINENSIS LEAF EXTRACT
CINNAMOMUM ZEYLANICUM BARK EXTRACT
ACORUS CALAMUS ROOT EXTRACT
COMMIPHORA MYRRHA RESIN EXTRACT
OLEA EUROPAEA FRUIT OIL
ARGANIA SPINOSA KERNEL OIL
LECITHIN
POLYGLYCERYL-3 DIISOSTEARATE
GLYCERIN
GLYCERYL STEARATE

WARNINGS

FLAMMABLE PRODUCT.
CONTENTS UNDER PRESSURE.

KEEP OUT OF THE CHILDREN